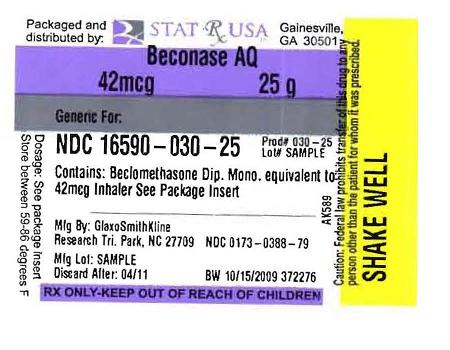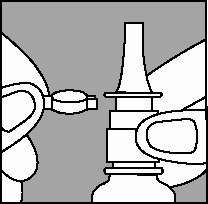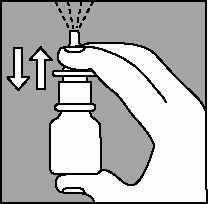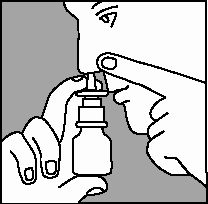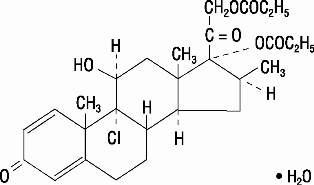 DRUG LABEL: BECONASE  
NDC: 16590-030 | Form: SPRAY, SUSPENSION
Manufacturer: Stat Rx USA LLC
Category: prescription | Type: HUMAN PRESCRIPTION DRUG LABEL
Date: 20100908

ACTIVE INGREDIENTS: BECLOMETHASONE DIPROPIONATE MONOHYDRATE  42 ug/1 1
INACTIVE INGREDIENTS: CELLULOSE, MICROCRYSTALLINE; CARBOXYMETHYLCELLULOSE SODIUM; DEXTROSE; BENZALKONIUM CHLORIDE; POLYSORBATE 80; PHENETHYL ALCOHOL

BECONASE (beclomethasone dipropionate monohydrate) spray, suspension

DESCRIPTION

Beclomethasone dipropionate, monohydrate, the active component of BECONASE AQ Nasal Spray, is an anti-inflammatory steroid having the chemical name 9-chloro-11β,17,21-trihydroxy-16β-methylpregna-1,4-diene-3,20-dione 17,21-dipropionate, monohydrate and the following chemical structure:

Beclomethasone 17,21-dipropionate is a diester of beclomethasone, a synthetic halogenated corticosteroid. Beclomethasone dipropionate, monohydrate is a white to creamy-white, odorless powder with a molecular weight of 539.06. It is very slightly soluble in water, very soluble in chloroform, and freely soluble in acetone and in ethanol.

BECONASE AQ Nasal Spray is a metered-dose, manual pump spray unit containing a microcrystalline suspension of beclomethasone dipropionate, monohydrate equivalent to 42 mcg of beclomethasone dipropionate, calculated on the dried basis, in an aqueous medium containing microcrystalline cellulose, carboxymethylcellulose sodium, dextrose, benzalkonium chloride, polysorbate 80, and 0.25% v/w phenylethyl alcohol. The pH through expiry is 5.0 to 6.8.

After initial priming (6 actuations), each actuation of the pump delivers from the nasal adapter 100 mg of suspension containing beclomethasone dipropionate, monohydrate equivalent to 42 mcg of beclomethasone dipropionate. If the pump is not used for 7 days, it should be primed until a fine spray appears. Each 25-g bottle of BECONASE AQ Nasal Spray provides 180 metered sprays.

CLINICAL PHARMACOLOGYMechanism of Action

Following topical administration, beclomethasone dipropionate produces anti-inflammatory and vasoconstrictor effects. The mechanisms responsible for the anti-inflammatory action of beclomethasone dipropionate are unknown. Corticosteroids have been shown to have a wide range of effects on multiple cell types (e.g., mast cells, eosinophils, neutrophils, macrophages, and lymphocytes) and mediators (e.g., histamine, eicosanoids, leukotrienes, and cytokines) involved in inflammation. The direct relationship of these findings to the effects of beclomethasone dipropionate on allergic rhinitis symptoms is not known.

Biopsies of nasal mucosa obtained during clinical studies showed no histopathologic changes when beclomethasone dipropionate was administered intranasally.

Beclomethasone dipropionate is a pro-drug with weak glucocorticoid receptor binding affinity. It is hydrolyzed via esterase enzymes to its active metabolite beclomethasone-17-monopropionate (B-17-MP), which has high topical anti-inflammatory activity.

Pharmacokinetics Absorption

Beclomethasone dipropionate is sparingly soluble in water. When given by nasal inhalation in the form of an aqueous or aerosolized suspension, the drug is deposited primarily in the nasal passages. The majority of the drug is eventually swallowed. Following intranasal administration of aqueous beclomethasone dipropionate, the systemic absorption was assessed by measuring the plasma concentrations of its active metabolite B-17-MP, for which the absolute bioavailability following intranasal administration is 44% (43% of the administered dose came from the swallowed portion and only 1% of the total dose was bioavailable from the nose). The absorption of unchanged beclomethasone dipropionate following oral and intranasal dosing was undetectable (plasma concentrations less than 50 pg/mL).

Distribution

The tissue distribution at steady state for beclomethasone dipropionate is moderate (20 L) but more extensive for B-17-MP (424 L). There is no evidence of tissue storage of beclomethasone dipropionate or its metabolites. Plasma protein binding is moderately high (87%).

Metabolism

Beclomethasone dipropionate is cleared very rapidly from the systemic circulation by metabolism mediated via esterase enzymes that are found in most tissues. The main product of metabolism is the active metabolite (B-17-MP). Minor inactive metabolites, beclomethasone-21-monopropionate (B-21-MP) and beclomethasone (BOH), are also formed, but these contribute little to systemic exposure.

Elimination

The elimination of beclomethasone dipropionate and B-17-MP after intravenous administration are characterized by high plasma clearance (150 and 120 L/hour) with corresponding terminal elimination half-lives of 0.5 and 2.7 hours. Following oral administration of tritiated beclomethasone dipropionate, approximately 60% of the dose was excreted in the feces within 96 hours, mainly as free and conjugated polar metabolites. Approximately 12% of the dose was excreted as free and conjugated polar metabolites in the urine. The renal clearance of beclomethasone dipropionate and its metabolites is negligible.

Pharmacodynamics

The effects of beclomethasone dipropionate on hypothalamic-pituitary-adrenal (HPA) function have been evaluated in adult volunteers by other routes of administration. Studies with beclomethasone dipropionate by the intranasal route may demonstrate that there is more or that there is less absorption by this route of administration. There was no suppression of early morning plasma cortisol concentrations when beclomethasone dipropionate was administered in a dose of 1,000 mcg/day for 1 month as an oral aerosol or for 3 days by intramuscular injection. However, partial suppression of plasma cortisol concentrations was observed when beclomethasone dipropionate was administered in doses of 2,000 mcg/day either by oral aerosol or intramuscular injection. Immediate suppression of plasma cortisol concentrations was observed after single doses of 4,000 mcg of beclomethasone dipropionate. Suppression of HPA function (reduction of early morning plasma cortisol levels) has been reported in adult patients who received 1,600-mcg daily doses of oral beclomethasone dipropionate for 1 month. In clinical studies using beclomethasone dipropionate aerosol intranasally, there was no evidence of adrenal insufficiency. The effect of BECONASE AQ Nasal Spray on HPA function was not evaluated but would not be expected to differ from intranasal beclomethasone dipropionate aerosol.

In 1 study in children with asthma, the administration of inhaled beclomethasone at recommended daily doses for at least 1 year was associated with a reduction in nocturnal cortisol secretion. The clinical significance of this finding is not clear. It reinforces other evidence, however, that topical beclomethasone may be absorbed in amounts that can have systemic effects and that physicians should be alert for evidence of systemic effects, especially in chronically treated patients (see PRECAUTIONS).

INDICATIONS AND USAGE

BECONASE AQ Nasal Spray is indicated for the relief of the symptoms of seasonal or perennial allergic and nonallergic (vasomotor) rhinitis.

Results from 2 clinical trials have shown that significant symptomatic relief was obtained within 3 days. However, symptomatic relief may not occur in some patients for as long as 2 weeks. BECONASE AQ Nasal Spray should not be continued beyond 3 weeks in the absence of significant symptomatic improvement. BECONASE AQ Nasal Spray should not be used in the presence of untreated localized infection involving the nasal mucosa.

BECONASE AQ Nasal Spray is also indicated for the prevention of recurrence of nasal polyps following surgical removal.

Clinical studies have shown that treatment of the symptoms associated with nasal polyps may have to be continued for several weeks or more before a therapeutic result can be fully assessed. Recurrence of symptoms due to polyps can occur after stopping treatment, depending on the severity of the disease.

CONTRAINDICATIONS

Hypersensitivity to any of the ingredients of this preparation contraindicates its use.

WARNINGS

The replacement of a systemic corticosteroid with BECONASE AQ Nasal Spray can be accompanied by signs of adrenal insufficiency.

Careful attention must be given when patients previously treated for prolonged periods with systemic corticosteroids are transferred to BECONASE AQ Nasal Spray. This is particularly important in those patients who have associated asthma or other clinical conditions where too rapid a decrease in systemic corticosteroids may cause a severe exacerbation of their symptoms.

If recommended doses of intranasal beclomethasone are exceeded or if individuals are particularly sensitive or predisposed by virtue of recent systemic steroid therapy, symptoms of hypercorticism may occur, including very rare cases of menstrual irregularities, acneiform lesions, cataracts, and cushingoid features. If such changes occur, BECONASE AQ Nasal Spray should be discontinued slowly consistent with accepted procedures for discontinuing oral steroid therapy.

Persons who are using drugs that suppress the immune system are more susceptible to infections than healthy individuals. Chickenpox and measles, for example, can have a more serious or even fatal course in susceptible children or adults using corticosteroids. In children or adults who have not had these diseases or been properly immunized, particular care should be taken to avoid exposure. How the dose, route, and duration of corticosteroid administration affect the risk of developing a disseminated infection is not known. The contribution of the underlying disease and/or prior corticosteroid treatment to the risk is also not known. If exposed to chickenpox, prophylaxis with varicella zoster immune globulin (VZIG) may be indicated. If exposed to measles, prophylaxis with pooled intramuscular immunoglobulin (IG) may be indicated. (See the respective package inserts for complete VZIG and IG prescribing information.) If chickenpox develops, treatment with antiviral agents may be considered.

Avoid spraying in eyes.

PRECAUTIONS

PRECAUTIONSGeneral

Intranasal corticosteroids may cause a reduction in growth velocity when administered to pediatric patients (see PRECAUTIONS: Pediatric Use).

During withdrawal from oral corticosteroids, some patients may experience symptoms of withdrawal, e.g., joint and/or muscular pain, lassitude, and depression.

Rarely, immediate hypersensitivity reactions may occur after the intranasal administration of beclomethasone (see ADVERSE REACTIONS).

Rare instances of nasal septum perforation have been spontaneously reported.

Rare instances of wheezing, cataracts, glaucoma, and increased intraocular pressure have been reported following the intranasal use of beclomethasone dipropionate.

In clinical studies with beclomethasone dipropionate administered intranasally, the development of localized infections of the nose and pharynx with Candida albicans has occurred only rarely. When such an infection develops, it may require treatment with appropriate local therapy and discontinuation of treatment with BECONASE AQ Nasal Spray.

If persistent nasopharyngeal irritation occurs, it may be an indication for stopping BECONASE AQ Nasal Spray.

Beclomethasone dipropionate is absorbed into the circulation. Use of excessive doses of BECONASE AQ Nasal Spray may suppress HPA function.

Intranasal corticosteroids should be used with caution, if at all, in patients with active or quiescent tuberculous infections of the respiratory tract, untreated local or systemic fungal or bacterial infections, systemic viral or parasitic infections, or ocular herpes simplex.

For BECONASE AQ Nasal Spray to be effective in the treatment of nasal polyps, the spray must be able to enter the nose. Therefore, treatment of nasal polyps with BECONASE AQ Nasal Spray should be considered adjunctive therapy to surgical removal and/or the use of other medications that will permit effective penetration of BECONASE AQ Nasal Spray into the nose. Nasal polyps may recur after any form of treatment.

As with any long-term treatment, patients using BECONASE AQ Nasal Spray over several months or longer should be examined periodically for possible changes in the nasal mucosa.

Because of the inhibitory effect of corticosteroids on wound healing, patients who have experienced recent nasal septal ulcers, nasal surgery, or nasal trauma should not use a nasal corticosteroid until healing has occurred.

Although systemic effects have been minimal with recommended doses, this potential increases with excessive doses. Therefore, larger than recommended doses should be avoided.

ADVERSE REACTIONS

In general, side effects in clinical studies have been primarily associated with irritation of the nasal mucous membranes.

Adverse reactions reported in controlled clinical trials and open studies in patients treated with BECONASE AQ Nasal Spray are described below.

Mild nasopharyngeal irritation following the use of beclomethasone aqueous nasal spray has been reported in up to 24% of patients treated, including occasional sneezing attacks (about 4%) occurring immediately following use of the spray. In patients experiencing these symptoms, none had to discontinue treatment. The incidence of transient irritation and sneezing was approximately the same in the group of patients who received placebo in these studies, implying that these complaints may be related to vehicle components of the formulation.

Fewer than 5 per 100 patients reported headache, nausea, or lightheadedness following the use of BECONASE AQ Nasal Spray. Fewer than 3 per 100 patients reported nasal stuffiness, nosebleeds, rhinorrhea, or tearing eyes.

Rare cases of ulceration of the nasal mucosa and instances of nasal septum perforation have been spontaneously reported (see PRECAUTIONS).

Reports of dryness and irritation of the nose and throat and unpleasant taste and smell have been received. There are rare reports of loss of taste and smell.

Rare instances of wheezing, cataracts, glaucoma, and increased intraocular pressure have been reported following the use of intranasal beclomethasone dipropionate (see PRECAUTIONS).

Rare cases of immediate and delayed hypersensitivity reactions, including anaphylactoid/anaphylactic reactions, urticaria, angioedema, rash, and bronchospasm, have been reported following the oral and intranasal inhalation of beclomethasone dipropionate.

Cases of growth suppression have been reported for intranasal corticosteroids, including BECONASE AQ (see PRECAUTIONS: Pediatric Use).

OVERDOSAGE

When used at excessive doses, systemic corticosteroid effects such as hypercorticism and adrenal suppression may appear. If such changes occur, BECONASE AQ Nasal Spray should be discontinued slowly consistent with accepted procedures for discontinuing oral steroid therapy. No deaths occurred when beclomethasone dipropionate was given as single oral doses of 3,000 mg/kg to mice (approximately 36,000 times the maximum recommended daily intranasal dose in adults on a mg/m^2 basis, or approximately 21,000 times the maximum recommended daily intranasal dose in children on a mg/m^2 basis) and 2,000 mg/kg to rats (approximately 48,000 times the maximum recommended daily intranasal dose in adults or approximately 29,000 times the maximum recommended daily intranasal dose in children on a mg/m^2 basis). One bottle of BECONASE AQ Nasal Spray contains beclomethasone dipropionate, monohydrate equivalent to 10.5 mg of beclomethasone dipropionate; therefore, acute overdosage is unlikely.

DOSAGE AND ADMINISTRATION

DOSAGE AND ADMINISTRATIONAdults and Children 12 Years of Age and Older

The usual dosage is 1 or 2 nasal inhalations (42 to 84 mcg) in each nostril twice a day (total dose, 168 to 336 mcg/day).

Children 6 to 12 Years of Age

Patients should be started with 1 nasal inhalation in each nostril twice daily; patients not adequately responding to 168 mcg or those with more severe symptoms may use 336 mcg (2 inhalations in each nostril). Once adequate control is achieved, the dosage should be decreased to 84 mcg (1 spray in each nostril) twice daily. BECONASE AQ Nasal Spray is not recommended for children below 6 years of age.

The maximum total daily dosage should not exceed 2 sprays in each nostril twice daily (336 mcg/day).

In patients who respond to BECONASE AQ Nasal Spray, an improvement of the symptoms of seasonal or perennial rhinitis usually becomes apparent within a few days after the start of therapy with BECONASE AQ Nasal Spray. However, symptomatic relief may not occur in some patients for as long as 2 weeks. BECONASE AQ Nasal Spray should not be continued beyond 3 weeks in the absence of significant symptomatic improvement.

The therapeutic effects of corticosteroids, unlike those of decongestants, are not immediate. This should be explained to the patient in advance in order to ensure cooperation and continuation of treatment with the prescribed dosage regimen.

In the presence of excessive nasal mucous secretion or edema of the nasal mucosa, the drug may fail to reach the site of intended action. In such cases it is advisable to use a nasal vasoconstrictor during the first 2 to 3 days of therapy with BECONASE AQ Nasal Spray.

Directions for Use

Illustrated Patient's Instructions for Use accompany each package of BECONASE AQ Nasal Spray.

HOW SUPPLIED

BECONASE AQ Nasal Spray, 42 mcg is supplied in an amber glass bottle fitted with a metering atomizing pump and nasal adapter in a box of 1 (NDC 0173-0388-79) with patient’s instructions for use. Each bottle contains 25 g of suspension and will provide 180 metered sprays.

The correct amount of medication in each spray cannot be assured after 180 sprays even though the bottle is not completely empty. The bottle should be discarded when the labeled number of actuations has been used.

Store between 15°and 30°C (59°and 86°F).

GlaxoSmithKline

Research Triangle Park, NC 27709

April 2005 RL-2182

Information for Patients

Patients being treated with BECONASE AQ Nasal Spray should receive the following information and instructions. This information is intended to aid them in the safe and effective use of this medication. It is not a disclosure of all possible adverse or intended effects.

Patients should use BECONASE AQ Nasal Spray at regular intervals since its effectiveness depends on its regular use. The patient should take the medication as directed. It is not acutely effective, and the prescribed dosage should not be increased. Instead, nasal vasoconstrictors or oral antihistamines may be needed until the effects of BECONASE AQ Nasal Spray are fully manifested. One to 2 weeks may pass before full relief is obtained. The patient should contact the physician if symptoms do not improve, if the condition worsens, or if sneezing or nasal irritation occurs.

For the proper use of BECONASE AQ Nasal Spray and to attain maximum improvement, the patient should read and follow carefully the patient's instructions accompanying the product.

Persons who are using immunosuppressant doses of corticosteroids should be warned to avoid exposure to chickenpox or measles. Patients should also be advised that if they are exposed, medical advice should be sought without delay.

Carcinogenesis, Mutagenesis, Impairment of Fertility

The carcinogenicity of beclomethasone dipropionate was evaluated in rats that were exposed for a total of 95 weeks, 13 weeks at inhalation doses up to 0.4 mg/kg and the remaining 82 weeks at combined oral and inhalation doses up to 2.4 mg/kg. There was no evidence of carcinogenicity in this study at the highest dose, approximately 60 times the maximum recommended daily intranasal dose in adults on a mg/m^2 basis or approximately 35 times the maximum recommended daily intranasal dose in children on a mg/m^2 basis.

Beclomethasone dipropionate did not induce gene mutation in bacterial cells or mammalian Chinese hamster ovary (CHO) cells in vitro. No significant clastogenic effect was seen in cultured CHO cells in vitro or in the mouse micronucleus test in vivo.

In rats, beclomethasone dipropionate caused decreased conception rates at an oral dose of 16 mg/kg (approximately 390 times the maximum recommended daily intranasal dose in adults on a mg/m^2 basis). There was no significant effect of beclomethasone dipropionate on fertility in rats at oral doses of 1.6 mg/kg (approximately 40 times the maximum recommended daily intranasal dose in adults on a mg/m^2 basis). Inhibition of the estrous cycle in dogs was observed following oral dosing at 0.5 mg/kg (approximately 40 times the maximum recommended daily intranasal dose in adults on a mg/m^2 basis). No inhibition of the estrous cycle in dogs was seen following 12 months’ exposure at an estimated inhalation dose of 0.33 mg/kg (approximately 25 times the maximum recommended daily intranasal dose in adults on a mg/m^2 basis).

Pregnancy Teratogenic Effects

Pregnancy Category C. Like other corticosteroids, beclomethasone dipropionate was teratogenic and embryocidal in the mouse and rabbit at a subcutaneous dose of 0.1 mg/kg in mice or 0.025 mg/kg in rabbits (approximately equal to the maximum recommended daily intranasal dose in adults on a mg/m^2 basis). No teratogenicity or embryocidal effects were seen in rats when exposed to an inhalation dose of 0.1 mg/kg plus oral doses of up to 10 mg/kg per day for a combined dose of 10.1 mg/kg (approximately 240 times the maximum recommended daily intranasal dose in adults on a mg/m^2 basis).

There are no adequate and well-controlled studies in pregnant women. Beclomethasone dipropionate should be used during pregnancy only if the potential benefit justifies the potential risk to the fetus.

Nonteratogenic Effects

Hypoadrenalism may occur in infants born of mothers receiving corticosteroids during pregnancy. Such infants should be carefully observed.

Nursing Mothers

It is not known whether beclomethasone dipropionate is excreted in human milk. Because other corticosteroids are excreted in human milk, caution should be exercised when BECONASE AQ Nasal Spray is administered to a nursing woman.

Pediatric Use

The safety and effectiveness of BECONASE AQ Nasal Spray have been established in children aged 6 years and above through evidence from extensive clinical use in adult and pediatric patients. The safety and effectiveness of BECONASE AQ Nasal Spray in children below 6 years of age have not been established.

Controlled clinical studies have shown that intranasal corticosteroids may cause a reduction in growth velocity in pediatric patients. This effect has been observed in the absence of laboratory evidence of HPA axis suppression, suggesting that growth velocity is a more sensitive indicator of systemic corticosteroid exposure in pediatric patients than some commonly used tests of HPA axis function. The long-term effects of this reduction in growth velocity associated with intranasal corticosteroids, including the impact on final adult height, are unknown. The potential for “catch-up” growth following discontinuation of treatment with intranasal corticosteroids has not been adequately studied. The growth of pediatric patients receiving intranasal corticosteroids, including BECONASE AQ Nasal Spray, should be monitored routinely (e.g., via stadiometry). The potential growth effects of prolonged treatment should be weighed against the clinical benefits obtained and the risks/benefits of treatment alternatives. To minimize the systemic effects of intranasal corticosteroids, including BECONASE AQ Nasal Spray, each patient should be titrated to the lowest dose that effectively controls his/her symptoms.

In a double-blind, controlled trial, 100 children between the ages of 6 and 9½ years with allergic rhinitis were randomized to receive aqueous intranasal beclomethasone dipropionate 168 mcg twice daily or placebo for 1 year. As measured by stadiometry, children who received beclomethasone dipropionate grew more slowly than those who received placebo. A difference in mean change in height was observed within 1 month of drug initiation. At the end of 12 months, the beclomethasone dipropionate-treated group had a growth velocity on average of 4.75 cm/year compared to 6.20 cm/year in the placebo group (p less than 0.01). While the placebo group had an expected distribution of growth velocity, approximately 50% of the beclomethasone dipropionate-treated children grew below the 10th percentile.

In children 7.3 years of age, the mean age of children in this study, the range for expected growth velocity is: boys − 3rd percentile = 4.1 cm/year, 50th percentile = 5.8 cm/year, and 97th percentile = 7.5 cm/year; girls − 3rd percentile = 4.3 cm/year, 50th percentile = 5.9 cm/year, and 97th percentile = 7.5 cm/year. The potential reversibility of the reduction in growth velocity was not studied. No significant differences were observed between the 2 groups for mean basal plasma cortisol or ACTH-stimulated plasma cortisol levels.

Geriatric Use

Clinical studies of BECONASE AQ Nasal Spray did not include sufficient numbers of subjects aged 65 and over to determine whether they respond differently from younger subjects. Other reported clinical experience has not identified differences in responses between the elderly and younger patients. In general, dose selection for an elderly patient should be cautious, starting at the low end of the dosing range, reflecting the greater frequency of decreased hepatic, renal, or cardiac function, and of concomitant disease or other drug therapy.

Patient's Instructions for Use

PHARMACIST—DETACH HERE AND GIVE INSTRUCTIONS TO PATIENT

_ _ _ _ _ _ _ _ _ _ _ _ _ _ _ _ _ _ _ _ _ _ _ _ _ _ _ _ _ _ _ _ _ _ _ _ _ _ _ _ _ _ _ _ _ _ _ _ _ _ _ _

BECONASE AQ®

(beclomethasone dipropionate,

monohydrate)

Nasal Spray, 42 mcg

For Intranasal Use Only. SHAKE WELL BEFORE USE.

Patient’s Instructions for Use

Shake the suspension spray bottle well before using it. Read complete instructionscarefully and use only as directed.

To Use:

1. Remove the safety clip and the plastic dust cap from the nasal applicator (Figure 1).

2. The very first time the spray is used, prime the pump into the air by pressing downward on the white collar, using your forefinger and middle finger while supporting the base of the bottle with your thumb. When you prime the pump for the first time, press down and release the pump 6 times or until a fine spray appears (Figure 2).

The pump is now ready for use. If the pump is not used for 7 days, prime until a fine spray appears.

3. Gently blow your nose to clear your nostrils. Close 1 nostril. Tilt your head forward slightly and, keeping the bottle upright, carefully insert the nasal applicator into the other nostril (Figure 3).

4. For each spray, press firmly downward once on the white collar, using your forefinger and middle finger while supporting the base of the bottle with your thumb. Avoid spraying in eyes. Breathe gently inward through the nostril.

5. Breathe out through your mouth.

6. Repeat steps 5 through 7 in the other nostril.

7. Replace the plastic dust cap and safety clip.

8. DISCARD THE BOTTLE AFTER the date calculated by your doctor or pharmacist. The correct amount of medication in each spray cannot be assured after 180 sprays even though the bottle is not completely empty. Discard the bottle after 180 sprays. Before the discard date you should consult your doctor to see if a refill is needed. Do not take extra doses or stop taking BECONASE AQ Nasal Spray without consulting your doctor.

Cleansing: To clean the nasal applicator, remove the plastic dust cap and safety clip and then press gently upward on the white collar to free the nasal applicator. Wash the applicator and dust cap with cold water. Dry and replace with the plastic dust cap and safety clip back in position.

If the nasal applicator becomes blocked, remove the dust cap, unscrew the complete pump mechanism, and soak the pump in warm water for a few minutes. Rinse with cold water, dry, refit to bottle, and reprime the pump.

Caution: BECONASE AQ Nasal Spray is not intended to give rapid relief of your nasal symptoms. BECONASE AQ Nasal Spray controls the underlying disorders responsible for your attacks, so it is important that you use it regularly at the times recommended by your doctor. The full benefit of BECONASE AQ Nasal Spray may take a few days to develop.

Storage: Store between 15° and 30°C (59° and 86°F).

GlaxoSmithKline

Research Triangle Park, NC 27709

April 2005 RL-2182

Principal Display Panel

NDC 0173-0388-79

Beconase AQ®

(beclomethasone dipropionate, monohydrate)

Nasal Spray, 42 mcg

25 g

180 Metered Sprays

Spray-For Intranasal Use Only

Rx only

Important: Read accompanying directions carefully.

See package insert for Dosage Information.

After initial priming (6 actuations), each actuation of the pump delivers 100 mg of aqueous suspension containing beclomethasone dipropionate, monohydrate equivalent to 42 mcg of beclomethasone dipropionate and microcrystalline cellulose, carboxymethylcellulose sodium, dextrose, benzalkonium chloride, polysorbate 80, and 0.25% v/w phenylethyl alcohol.

Store between 15o and 30oC (59o and 86oF). Shake well before each use.

GlaxoSmithKline

Research Triangle Park, NC 27709

Made in Canada

A018016 Rev. 7/05

Label Image